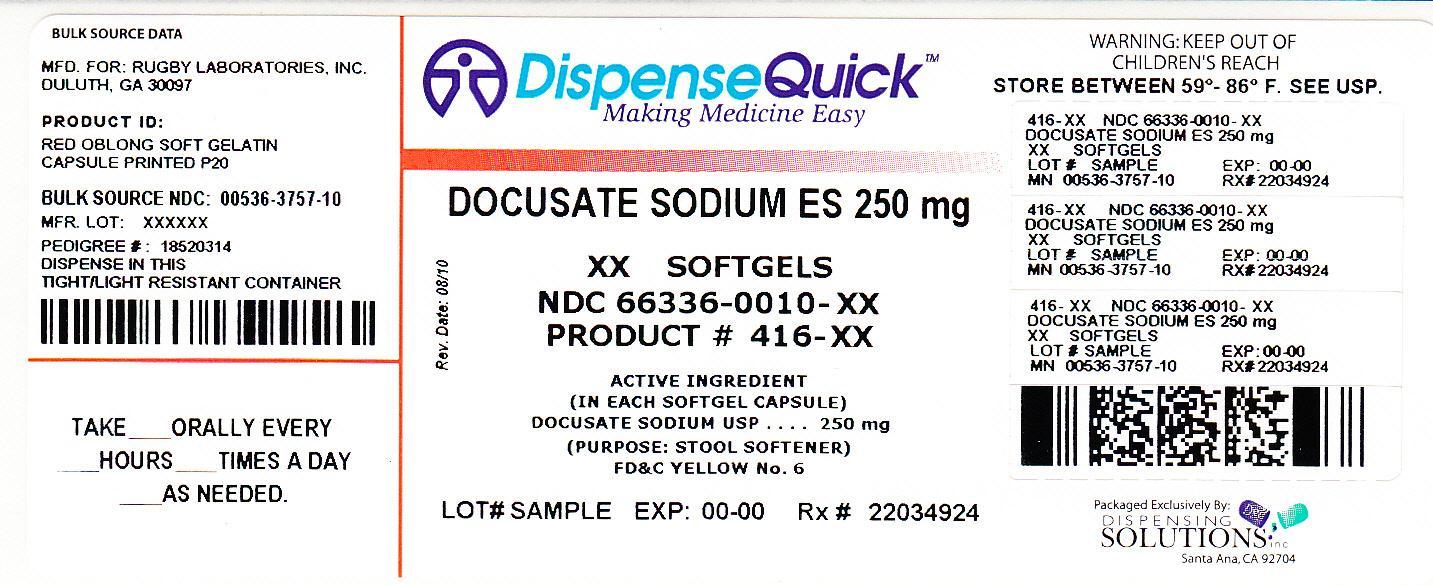 DRUG LABEL: EXTRA STRENGTH STOOL SOFTENER LAXATIVE
NDC: 66336-010 | Form: CAPSULE, LIQUID FILLED
Manufacturer: Dispensing Solutions, Inc.
Category: otc | Type: HUMAN OTC DRUG LABEL
Date: 20120914

ACTIVE INGREDIENTS: DOCUSATE SODIUM 250 mg/1 1
INACTIVE INGREDIENTS: FD&C RED NO. 40; FD&C YELLOW NO. 6; GELATIN; GLYCERIN; POLYETHYLENE GLYCOLS; PROPYLENE GLYCOL; WATER; SORBITOL

Docusate Sodium ES

Active Ingredient (in each softgel)

Docusate Sodium 250mg

Purpose

Stool softener

Uses

- Relieves occasional constipation.
- Generally produces bowel movement within 12 to72 hours.

Warnings - Do not use

- for longer than one week
- if you are taking mineral oil
- when abdominal pain, nausea, or vomiting are present

Ask a doctor before use if

you have a sudden change in bowel habits that lasts over two weeks

Ask a doctor or pharmacist before use if you are taking any other drug. Take this product two or more hours before or after other drugs. Laxatives may affect how other drugs work.

Stop use and ask a doctor if

- you experience rectal bleeding
- you fail to have a bowel movement after using this product

These may indicate a serious condition.

If pregnant or breastfeeding

ask a health professional before use.

Keep out of reach of children.

In case of overdose, get medical help or contact a Poison Control Center right away.

Directions

- adults and children over 12 years and over:1 capsule once daily
- children under 12 years: ask a doctor

Other information

- store at controlled room temperature 15 - 30 degrees C (59-86 degrees F)

Each capsule contains sodium 15mg

Inactive Ingredients

edible white ink, FDandC Red No. 40, FDandC Yellow No. 6, gelatin, glycerin, polyethylene glycol, propylene glycol, purified wter, sorbitol special.

Questions or comments?

Call 1-800-645-2158, 9am - 5am ET Monday - Friday

Product Labeling

Rugby Extra Strength Stool Softener Laxative
Docusate Sodium USP, 250mg
Mfd for: Rugby Laboratories, Inc
Duluth Georgia 30097
www.rugbylaboratories.com

Package Label

NDC 66336-0010-XX